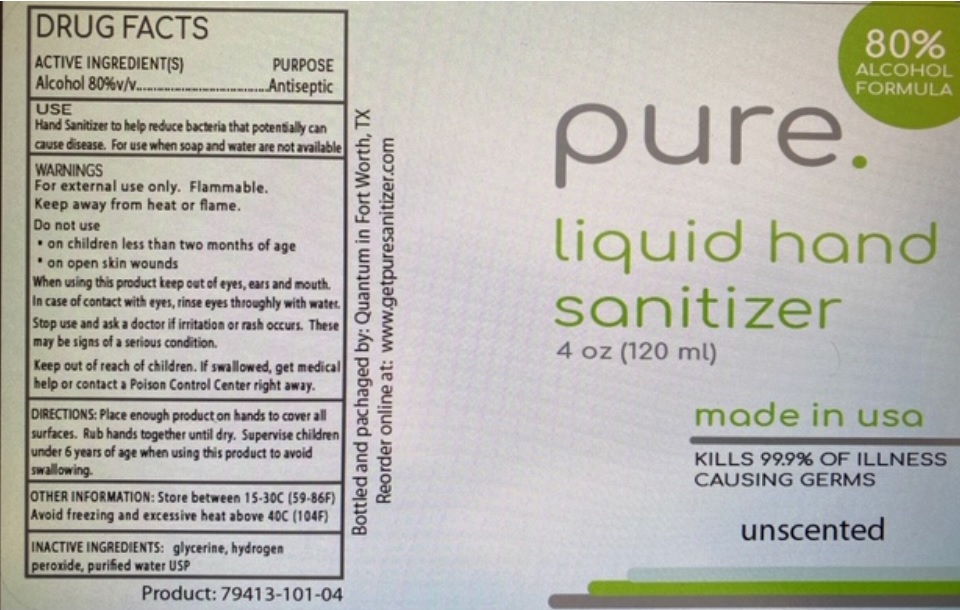 DRUG LABEL: Quantum Liquid Hand Sanitizer
NDC: 79413-101 | Form: LIQUID
Manufacturer: Quantum Valve And Oilfield Solutions, Llc
Category: otc | Type: HUMAN OTC DRUG LABEL
Date: 20200727

ACTIVE INGREDIENTS: ALCOHOL 80 mL/100 mL
INACTIVE INGREDIENTS: GLYCERIN; HYDROGEN PEROXIDE; WATER

pure. liquid hand sanitizer

ACTIVE INGREDIENTS(S)

Alcohol 80%v/v

PURPOSE

Antiseptic

USE

Hand sanitizer to help reduce bacteria that potentially can cause disease. For use when soap and water are not available

WARNINGS

For external use only. Flammable.

Keep away from heat or flame.

Do not use

• on children less than two months of age

• on open skin wounds

When using this product keep out of eyes, ears and mouth.

In case of contact with eyes, rinse eyes thoroughly with water.

Stop use and ask a doctor if irritation or rash occurs. These may be signs of a serious condition.

Keep out of reach of children. If swallowed, get medical help or contact a Poison Control Center right away.

DOSAGE AND ADMINISTRATION

DIRECTIONS: Place enough product on hands to cover all surfaces. Rub hands together until dry. Supervise children under 6 years of age when using this product to avoid swallowing.

OTHER INFORMATION: Store between 15-30C (59-86F)

Avoid freezing and excessive heat above 40C (104F)

INACTIVE INGREDIENTS: glycerin, hydrogen peroxide, purified water USP

80% ALCOHOL FORMULA

made in usa

KILLS 99.9% OF ILLNESS CAUSING GERMS

unscented

Bottled and packaged by: Quantum in Fort Worth, TX

Reorder online at: www.getpuresanitizer.com